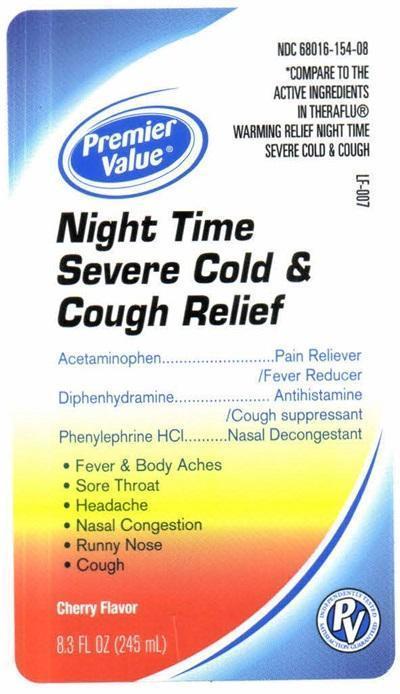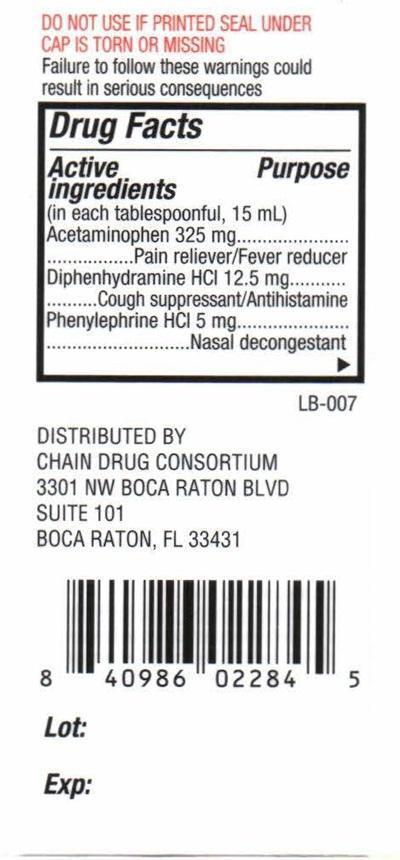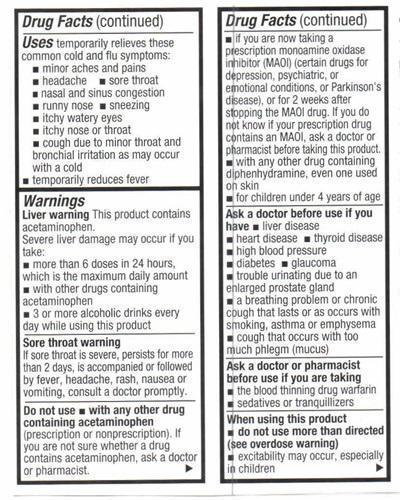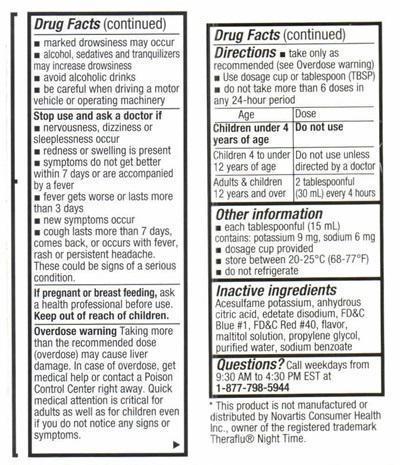 DRUG LABEL: Night Time Severe Cold and Cough Relief
NDC: 68016-154 | Form: LIQUID
Manufacturer: Chain Drug Consortium, LLC
Category: otc | Type: HUMAN OTC DRUG LABEL
Date: 20241229

ACTIVE INGREDIENTS: ACETAMINOPHEN 325 mg/15 mL; DIPHENHYDRAMINE HYDROCHLORIDE 12.5 mg/15 mL; PHENYLEPHRINE HYDROCHLORIDE 5 mg/15 mL
INACTIVE INGREDIENTS: ACESULFAME POTASSIUM; ANHYDROUS CITRIC ACID; EDETATE DISODIUM; FD&C BLUE NO. 1; FD&C RED NO. 40; MALTITOL; PROPYLENE GLYCOL; WATER; SODIUM BENZOATE

Drug facts Active ingredients

Active ingredients
(in each tablespoonful 15 mL)

Acetaminophen 325 mg
Diphenhydramine HCL 12.5 mg
Phenylephrine HCL 5mg

Purpose

Pain reliever/Fever reducer
Cough suppressant/Antihistamine
Nasal decongestant

Keep out of reach of children

Uses

temporarily relieves these common cold and flu symptoms:

- minor aches and pains
- headache
- sore throat
- nasal and sinus congestion
- runny nose
- sneezing
- itchy watery eyes
- itchy nose or throat
- cough due to minor throat and bronchial irritation as may occur with a cold
- temporarily reduces fever

Warnings

Liver warnings: This product contains acetaminophen.
Severe liver damage may occur if you take:

- more than 6 dose in 24 hours, which is the maximum daily amount
- with other drugs containing acetaminophen
- 3 or more alcoholic drinks daily while using this product

Warnings

Sore throat warning
If sore throat is severe, persists for more than 2 days, is accompanied or followed by fever, headache, rash, nausea or vomiting, consult a doctor promptly.

Do not use

- with any other drug containing acetaminophen (prescription or nonprescription). If you are not sure whether a drug contains acetaminophen, ask a doctor or pharmacist.
- if you are taking a prescription monamine oxidase inhibitor (MAOI) (certain drugs for depression, psychiatric, or emotional conditions, or Parkinson's disease), or for 2 weeks after stopping the MAOI drug. If you do not know if your prescription drug contains an MAOI, ask a doctor or pharmacist before taking this product
- with any other drug containing diphenhydramine, even one used on the skin
- for children under 4 years of age

Ask a doctor before use if you have

- liver disease
- heart disease
- thyroid disease
- high blood pressure
- diabetes
- trouble urinating due to an enlarged prostate gland
- a breathing problem or chronic cough that lasts or as occurs with smoking, asthma or empysema
- cough that occurs with too much phlegm (mucus)

Ask a doctor or pharmacist before use if you are taking

- the blood thinning drug warfarin
- sedatives or tranquilizers

When using this product

- do not use more than directed (see overdose warning)
- excitability may occur, especially in children
- marked drowsiness may occur
- alcohol, sedatives, and tranquilizers may increase drowsiness
- avoid alcohol drinks
- be careful when driving a motor vehicle or operating machinery

Stop use and ask a doctor if

- nervousness, dizziness or sleeplessness occur
- redness or swelling is present
- symptoms do not get better within 7 days or are accompanied by a fever
- fever gets worse or lasts more than 3 days
- new symptoms occur
- cough lasts more than 7 days, comes back, or occurs with fever, rash or persistent headache. These could be signs of a serious condition.

If pregnant or breast feeding

ask a health professional before use.

Overdose warning

Taking more than the recommended dose (overdose) may cause liver damage. In case of overdose, get medical help or contact the Poison Control Center right away. Quick medical attention is critical for adults as well as for children even if you do not notice any signs or symptoms.

Directions

Age Dose
Children under 4 years Do not use
Children 4 to under 12 years of age Do not use unless directed by a doctor
Adults and children 12 years and over 2 tablespoonful (30 mL) every 4 hours

- take only as recommended (see Overdose warning)
- use dose cup or tablespoon (TBSP)
- do not take more than 6 doses in any 24-hour period

Other information

- each tablespoon (15 mL) contains: potassium 9 mg, sodium 6 mg
- dosage cup provided
- store between 20°-25° C (68°-7°7 F)
- do not refrigerate

Inactive ingredients

Acesulfame potassium, anhydrous citric acid, edetate disodium, FD and C Blue #1, FD and C Red #40, flavor, maltitol solution, propylene glycol, purified water, sodium benzoate

Questions?

Call weekdays from 9:30 AM to 4:30 PM EST at 1-877-798-5944

Product Label

NDC 6801-154-08
*COMPARE TO THE ACTIVE INGREDIENTS IN THERAFUL® WARMING RELIEF COLD AND CHEST CONGESTION
Premier Value®
Night Time Severe Cold and Cough Relief
Acetaminophen ............ Pain Reliever/Fever Reducer
Diphenhydramine.......... Antihistamine/Cough Suppressant
Phenylephrine HCL ...... Nasal Congestion
Fever and Body Aches
Sore Throat
Headache
Nasal Congestion
Runny Nose
Cough

Cherry Flavor
8.3 FL OZ (245 mL)
PV Independently Tested Satisfaction Guaranteed
LF-007
DO NOT USE IF PRINTED SEAL UNDER AP IS TORN OR MISSING
Failure to follow these warnings could result in consequences
LB-007
DISTRIBUTED BY CHAIN DRUG CONSORTIUM
3301 NW BOCA RATON BLVD SUITE 101
BOCA RATON, FL 33431
Lot:
Exp:
*This product is not manufactured or distributed b Novartis Consumer health Inc., owner of the registered trademark Theraflu® Night Time